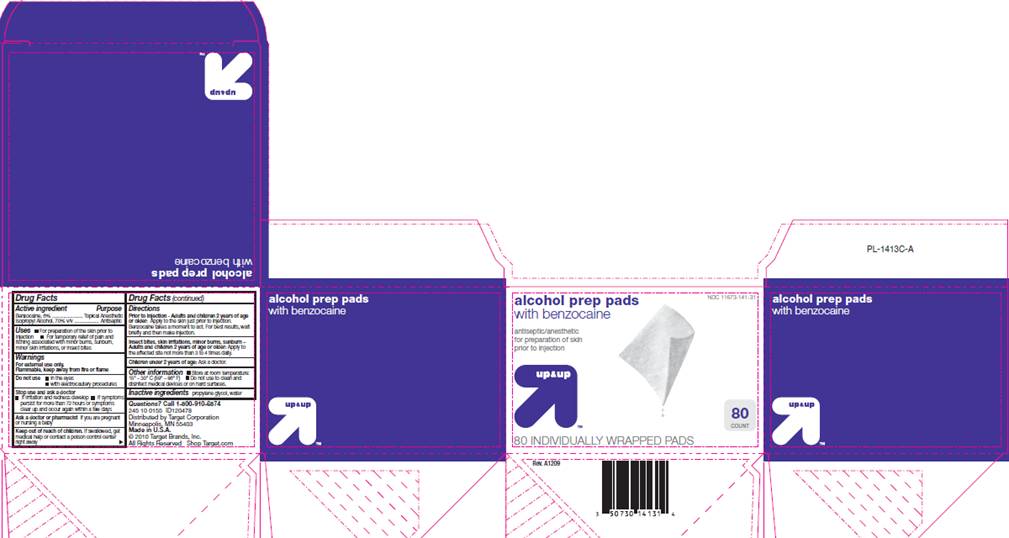 DRUG LABEL: Alcohol Prep Pads
NDC: 11673-141 | Form: SWAB
Manufacturer: Target Corporation
Category: otc | Type: HUMAN OTC DRUG LABEL
Date: 20100919

ACTIVE INGREDIENTS: benzocaine 0.06 mL/1 1; isopropyl alcohol 0.70 mL/1 1
INACTIVE INGREDIENTS: propylene glycol; water

DRUG FACTS

ACTIVE INGREDIENTS

Benzocaine 6%
Isopropyl alcohol 70% v/v

PURPOSE

Topical Anesthetic

Antiseptic

USES

- For preparation of the skin prior to injection
- For temporary relief of pain and itching associated with minor burns, sunburn, minor skin irritations, or insect bites

WARNINGS

For external use only.
Flammable, keep away from fire or flame.

Do not use

- in the eyes
- with electrocautery procedures

Stop use and ask a doctor

- if irritation and redness develop
- if symptoms persist for more than 72 hours or symptoms clear up and occur within a few days.

Ask a doctor or pharmacist

if you are pregnant or nursing a baby.

Keep out of reach of children

If swallowed, get medical help or contact a Poison Control Center right away.

DIRECTIONS

Prior to Injection - Adults and children 2 years of age or older:
Apply to the skin just prior to injection. Benzocaine takes a minute to act. for best results, wait briefly and then make injection.
Insect bites, skin irritations, minor burns, sunburn -
Adults and children 2 years of age or older:
Apply to the affected site not more than 3 to 4 times daily.
Children under 2 years of age: Ask a doctor.

OTHER INFORMATION

- Store at room temperature: 15° - 30° C (59° - 86° F)
- Do not use to clean and disinfect medical devices or on hard surfaces

INACTIVE INGREDIENTS

propylene glycol, water

Questions?

Call 1-800-910-6874

PACKAGE INFORMATION

NDC 11673-141-31

alcohol prep pads
with benzocaine

antiseptic/anesthetic
for preparation of the skin
prior to injection
up and up
80 count
80 INDIVIDUALLY WRAPPED PADS
245 10 0155 ID120478
Distributed by Target Corporation
Minneapolis, MN 55403
Made in U.S.A
©2010 Target Brands, Inc.

All Rights Reserved. Shop Target.com